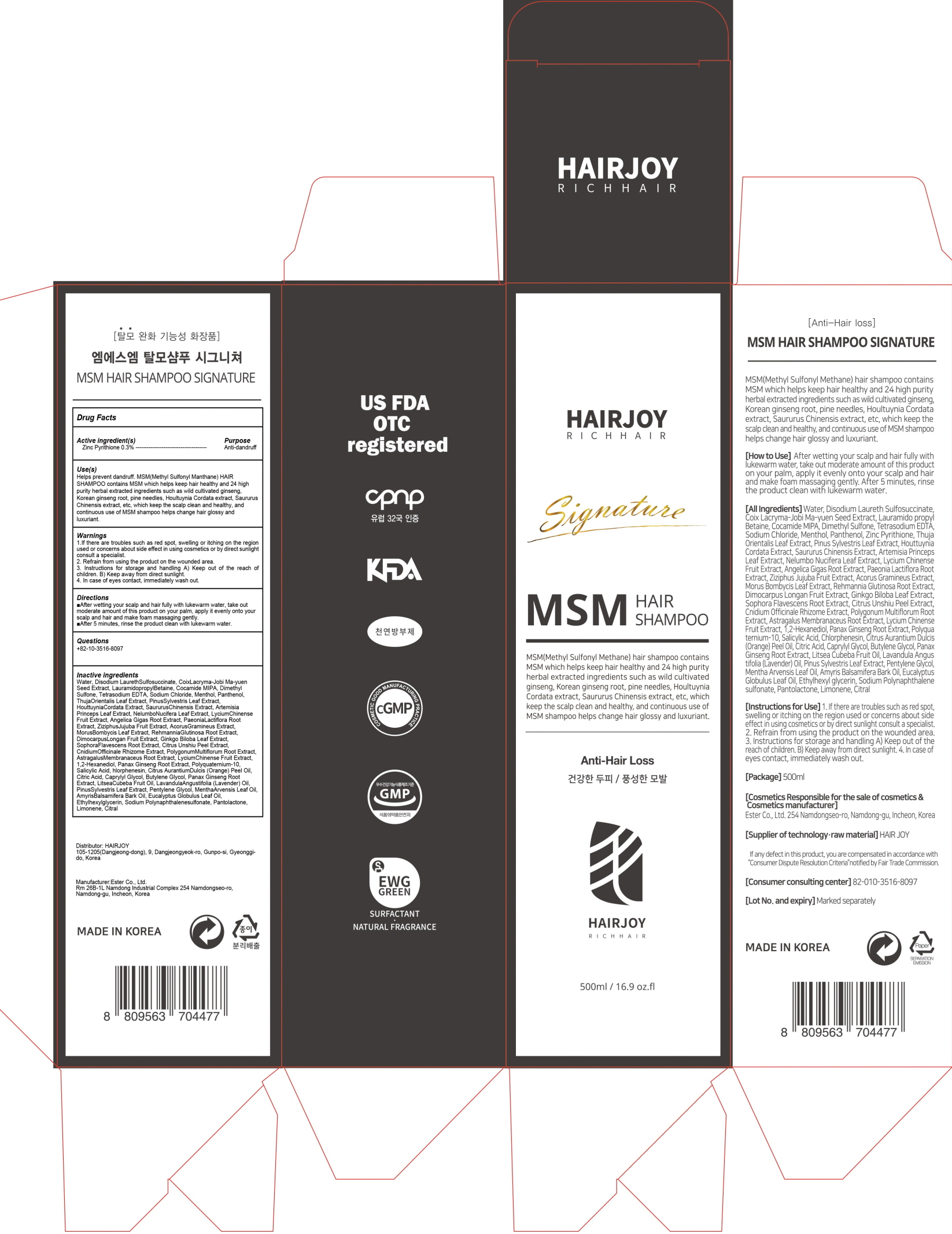 DRUG LABEL: MSM HAIR SIGNATURE
NDC: 69384-060 | Form: SHAMPOO
Manufacturer: HAIRJOY
Category: otc | Type: HUMAN OTC DRUG LABEL
Date: 20200825

ACTIVE INGREDIENTS: PYRITHIONE ZINC 1.5 g/500 mL
INACTIVE INGREDIENTS: Water; Dimethyl Sulfone

ACTIVE INGREDIENT

Zinc Pyrithione 0.3%

INACTIVE INGREDIENTS

Water, Disodium LaurethSulfosuccinate, CoixLacryma-Jobi Ma-yuen Seed Extract, LauramidopropylBetaine, Cocamide MIPA, Dimethyl Sulfone, Tetrasodium EDTA, Sodium Chloride, Menthol, Panthenol, ThujaOrientalis Leaf Extract, PinusSylvestris Leaf Extract, HouttuyniaCordata Extract, SaururusChinensis Extract, Artemisia Princeps Leaf Extract, NelumboNucifera Leaf Extract, LyciumChinense Fruit Extract, Angelica Gigas Root Extract, PaeoniaLactiflora Root Extract, ZiziphusJujuba Fruit Extract, AcorusGramineus Extract, MorusBombycis Leaf Extract, RehmanniaGlutinosa Root Extract, DimocarpusLongan Fruit Extract, Ginkgo Biloba Leaf Extract, SophoraFlavescens Root Extract, Citrus Unshiu Peel Extract, CnidiumOfficinale Rhizome Extract, PolygonumMultiflorum Root Extract, AstragalusMembranaceus Root Extract, LyciumChinense Fruit Extract, 1,2-Hexanediol, Panax Ginseng Root Extract, Polyquaternium-10, Salicylic Acid, hlorphenesin, Citrus AurantiumDulcis (Orange) Peel Oil, Citric Acid, Caprylyl Glycol, Butylene Glycol, Panax Ginseng Root Extract, LitseaCubeba Fruit Oil, LavandulaAngustifolia (Lavender) Oil, PinusSylvestris Leaf Extract, Pentylene Glycol, MenthaArvensis Leaf Oil, AmyrisBalsamifera Bark Oil, Eucalyptus Globulus Leaf Oil, Ethylhexylglycerin, Sodium Polynaphthalenesulfonate, Pantolactone, Limonene, Citral

PURPOSE

Anti-dandruff

WARNINGS

1.If there are troubles such as red spot, swelling or itching on the region used or concerns about side effect in using cosmetics or by direct sunlight consult a specialist.
2. Refrain from using the product on the wounded area.
3. Instructions for storage and handling A) Keep out of the reach of children. B) Keep away from direct sunlight.
4. In case of eyes contact, immediately wash out.

KEEP OUT OF REACH OF CHILDREN

Uses

Helps prevent dandruff. MSM(Methyl Sulfonyl Manthane) HAIR SHAMPOO contains MSM which helps keep hair healthy and 24 high purity herbal extracted ingredients such as wild cultivated ginseng, Korean ginseng root, pine needles, Houltuynia Cordata extract, Saururus Chinensis extract, etc, which keep the scalp clean and healthy, and continuous use of MSM shampoo helps change hair glossy and luxuriant.

Directions

■After wetting your scalp and hair fully with lukewarm water, take out moderate amount of this product on your palm, apply it evenly onto your scalp and hair and make foam massaging gently.
■After 5 minutes, rinse the product clean with lukewarm water.

QUESTIONS

+82-10-3516-8097